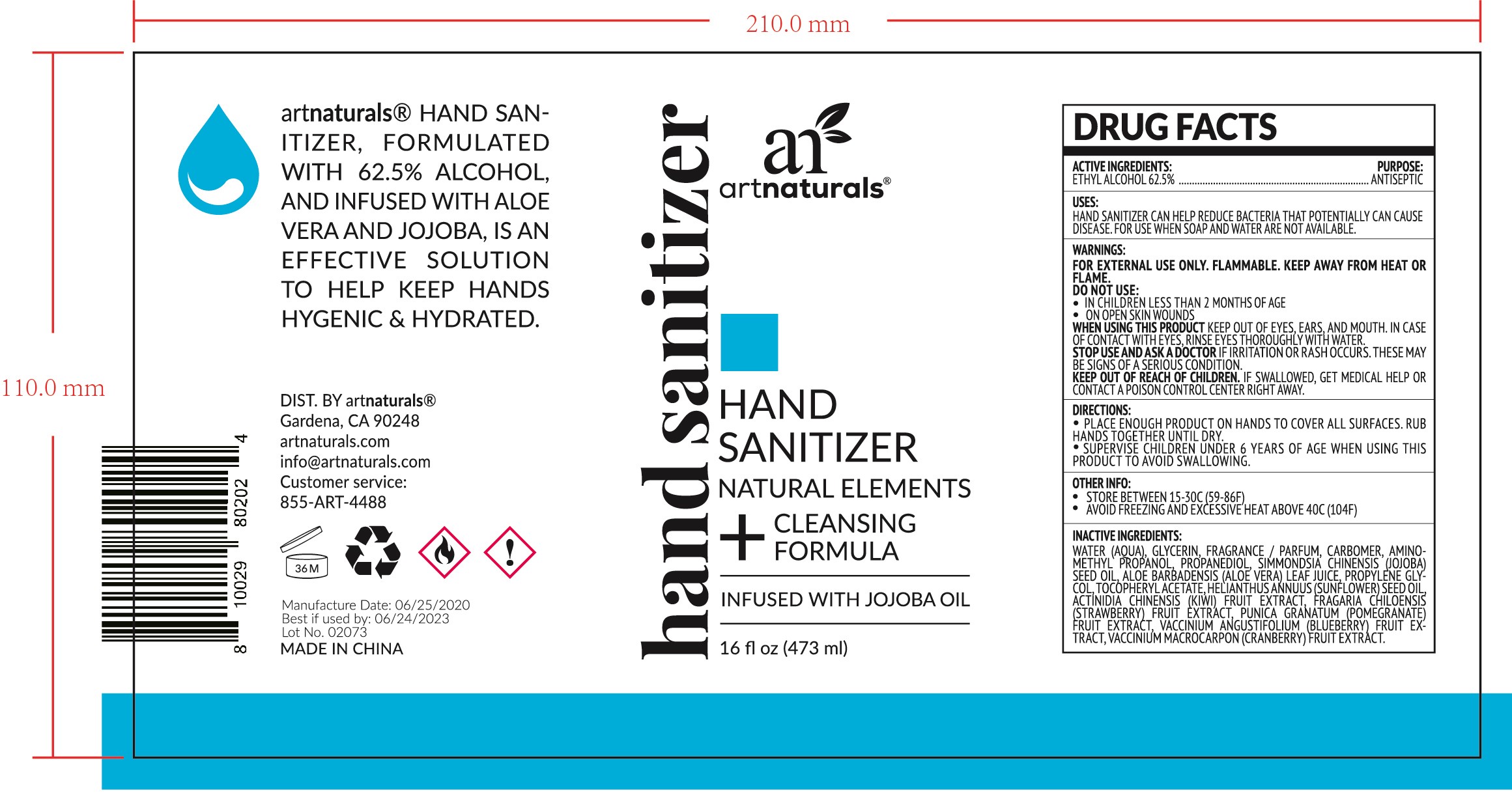 DRUG LABEL: HAND SANITIZER
NDC: 47993-285 | Form: GEL
Manufacturer: NINGBO JIANGBEI OCEAN STAR TRADING CO.,LTD
Category: otc | Type: HUMAN OTC DRUG LABEL
Date: 20201105

ACTIVE INGREDIENTS: ALCOHOL 62.5 g/112 mL
INACTIVE INGREDIENTS: WATER; GLYCERIN; CARBOMER 940; AMINOMETHYLPROPANOL; PROPANEDIOL; JOJOBA OIL; ALOE VERA LEAF; PROPYLENE GLYCOL; .ALPHA.-TOCOPHEROL ACETATE; SUNFLOWER OIL; KIWI FRUIT; FRAGARIA VESCA LEAF; PUNICA GRANATUM LEAF; VACCINIUM ANGUSTIFOLIUM LEAF; CRANBERRY JUICE

47993-285

Active ingredients

Ethyl Alcohol 62.5%

PURPOSE

Antiseptic

Uses：

Hand sanitizer can help reduce bacteria that potentially can cause disease. For use when soap and water are not available.

Warnings:

For external use only. Flammable. Keep away from heat or flame.

Do not use：

- In children less than 2 months of age.
- On open skin wounds.

When using this product keep out of eyes, ears, and mouth. In case of contact with eyes, rinse eyes thoroughly with water.

Stop use and ask a doctor if irritation or rash occurs. These may be signs of a serious condition.

Keep out of reach of children. If swallowed, get medical help or contact a Poison Control Center right away.

Directions:

- Place enough product on hands to cover all surfaces. Rub hands together until dry.
- Surpervise children under 6 years of age when using this product to avoid swallowing.

Other info:

- Store between 15-30℃（59-86℉）
- Avoid freezing and excessive heat above 40℃（104℉）

Inactive Ingredients:

Water (Aqua), Glycerin, Fragrance / Parfum, Carbomer, Aminomethyl propanol, Propanediol, Simmondsia chinensis (jojoba) seed oil, Aloe barbadensis (aloe vera) leaf juice, Propylene glycol, Tocopheryl acetate, Helianthus annuus (sunflower) seed oil, Actinidia chinesis (kiwi) fruit extract, Fragaria chiloensis (strawberry) fruit extract, Punica granatum (pomegranate) fruit extract, Vaccinium angustifolium (blueberry) fruit extract, Vaccinium macrocarpon (cranberry) fruit extract.